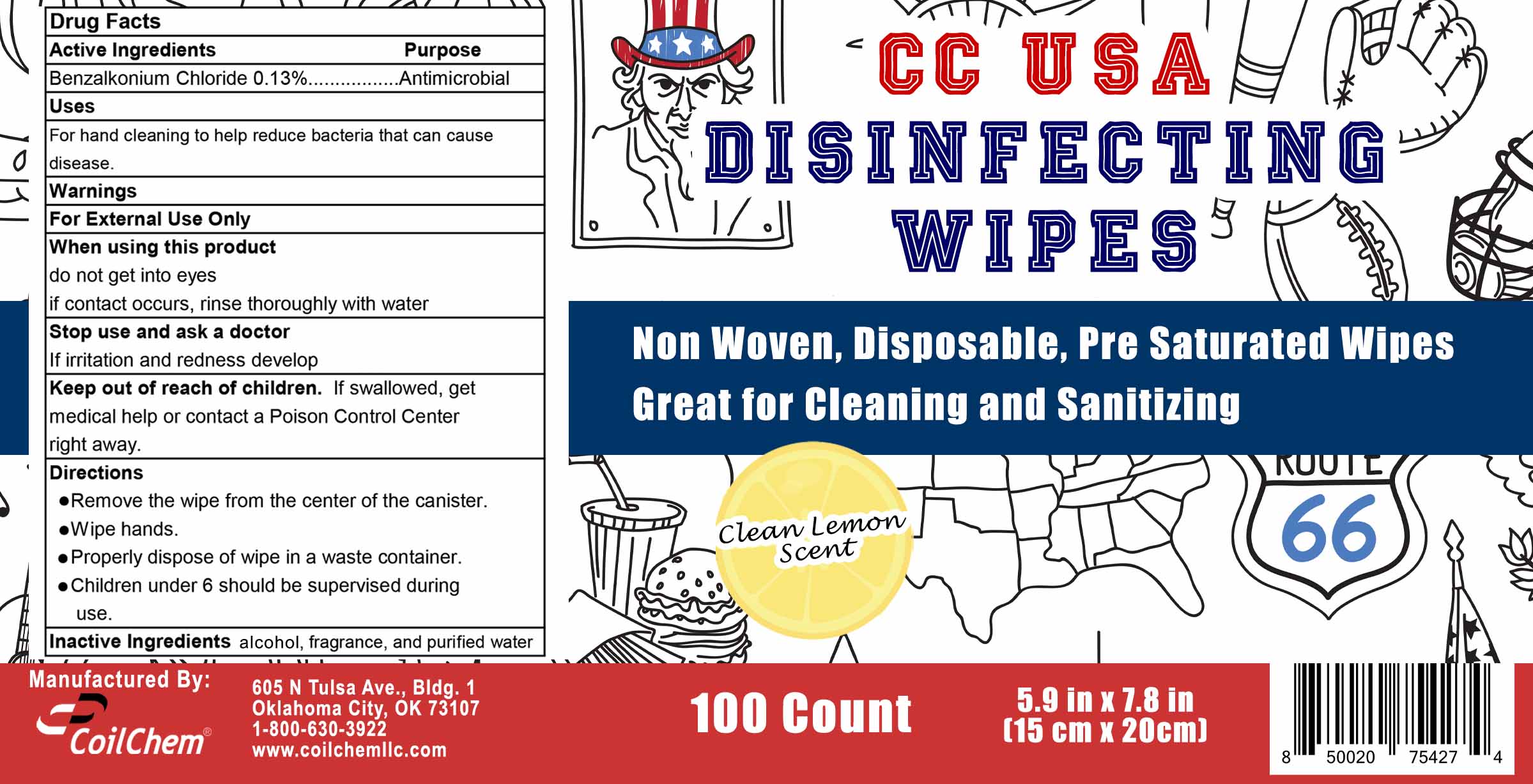 DRUG LABEL: CC USA Disinfecting Wipes
NDC: 75508-006 | Form: SOLUTION
Manufacturer: Coil Chem LLC
Category: otc | Type: HUMAN OTC DRUG LABEL
Date: 20201104

ACTIVE INGREDIENTS: BENZALKONIUM CHLORIDE 0.13 mg/100 mL
INACTIVE INGREDIENTS: FRAGRANCE LEMON ORC2001060 0.3 mL/100 mL; ALCOHOL 8 mL/100 mL; WATER 91.57 mL/100 mL

Active Ingredients

Benzalkonium Chloride 0.13%

Purpose

Antimicrobial

Uses

For hand cleaning to help reduce bacteria that can cause disease.

Warnings

For External Use Only

When using this product

do not get into eyes

if contact occurs, rinse thoroughly with water

Stop use and ask a doctor

If irritation and redness develop

Stop use and ask doctor

If irritation and redness develop

Keep out of reach of children.

If swallowed, get medical help or contact Poison Control Center right away.

Directions

- Remove the wipe from the center of the canister.
- Wipe hands.
- Properly dispose of wipe in a waste container.
- Children under 6 should be supervised during use.

Inactive Ingredients

ethanol, fragrance, and purified water

Package Label - Principal Display Panel

1 (100 ct) 75508-006-01